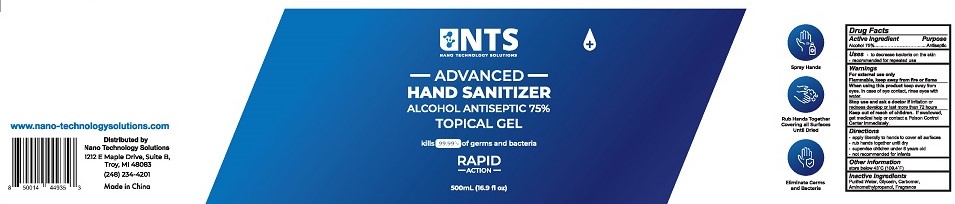 DRUG LABEL: NTS Advanced Hand Sanitizer
NDC: 76537-003 | Form: GEL
Manufacturer: Nano Technology Solutions
Category: otc | Type: HUMAN OTC DRUG LABEL
Date: 20200526

ACTIVE INGREDIENTS: ALCOHOL 75 mL/100 mL
INACTIVE INGREDIENTS: AMINOMETHYLPROPANOL; WATER; GLYCERIN; CARBOMER HOMOPOLYMER, UNSPECIFIED TYPE

NTS Advanced Hand Sanitizer Gel 75%

Drug Facts

Active ingredient

Alcohol 75%

Purpose
Antiseptic

Uses

- to decrease bacteria on the skin
- recommended for repeated use

Warnings
For external use only.
Flammable. Keep away from fire or flame.

When using this product keep away from eyes. In case of eye contact, rinse eyes with water.

Stop use and ask a doctor if irritation or redness develop or last more than 72 hours.

Keep out of reach of children. If swallowed, get medical help or contact a Poison Control Center immediately.

Directions

- apply liberally to hands to cover all surfaces
- rub hands together until dry
- supervise children under 6 years old
- not recommended for infants

Other information

store below 43°C (109.4°F)

Inactive ingredients

Purified Water , Glycerin, Carbomer, Aminomethylpropanol, Fragrance

Distributed by:

NANO TECHNOLOGY SOLUTIONS

1212 Maple Drive, Suite B

Troy, MI 48083

(248) 234-4201

Made in China

PACKAGE LABEL

NTS
NANO TECHNOLOGY SOLUTIONS
ADVANCED HAND SANITIZER
ALCOHOL ANTISEPTIC 75%

TOPICAL GEL
Kills 99.99% of germs and bacteria
RAPID ACTION
500 mL (16.9 fl oz)